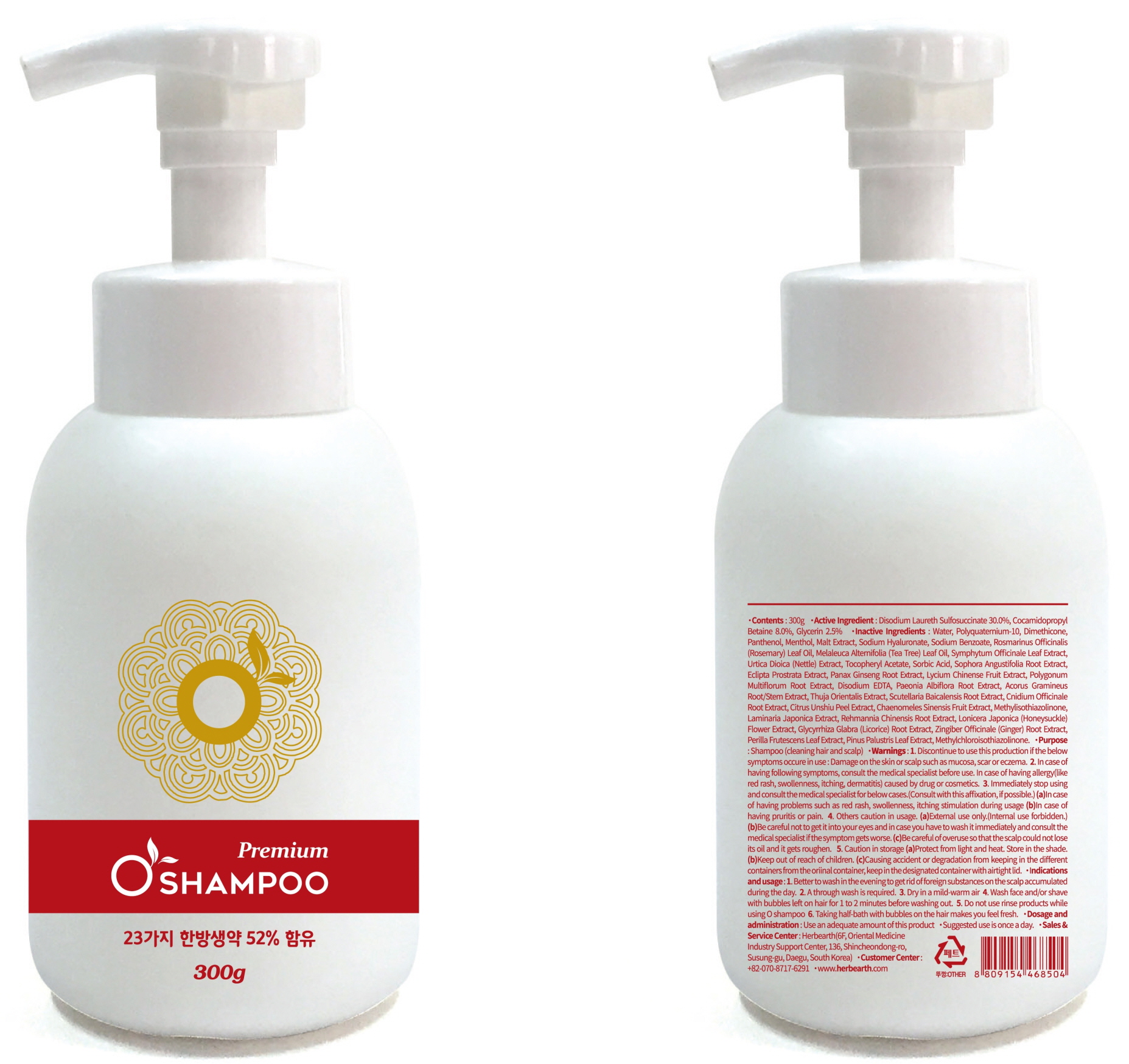 DRUG LABEL: O Sha mpoo Premium
NDC: 71043-010 | Form: SHAMPOO
Manufacturer: Herbearth
Category: otc | Type: HUMAN OTC DRUG LABEL
Date: 20161028

ACTIVE INGREDIENTS: GLYCERIN 7.5 g/300 g
INACTIVE INGREDIENTS: Water; Dimethicone

ACTIVE INGREDIENT

Active Ingredient: Disodium Laureth Sulfosuccinate 30.0%, Cocamidopropyl Betaine 8.0%, Glycerin 2.5%

INACTIVE INGREDIENT

Inactive Ingredients: Water, Polyquaternium-10, Dimethicone, Panthenol, Menthol, Malt Extract, Sodium Hyaluronate, Sodium Benzoate, Rosmarinus Officinalis (Rosemary) Leaf Oil, Melaleuca Alternifolia (Tea Tree) Leaf Oil, Symphytum Officinale Leaf Extract, Urtica Dioica (Nettle) Extract, Tocopheryl Acetate, Sorbic Acid, Sophora Angustifolia Root Extract, Eclipta Prostrata Extract, Panax Ginseng Root Extract, Lycium Chinense Fruit Extract, Polygonum Multiflorum Root Extract, Disodium EDTA, Paeonia Albiflora Root Extract, Acorus Gramineus Root/Stem Extract, Thuja Orientalis Extract, Scutellaria Baicalensis Root Extract, Cnidium Officinale Root Extract, Citrus Unshiu Peel Extract, Chaenomeles Sinensis Fruit Extract, Methylisothiazolinone, Laminaria Japonica Extract, Rehmannia Chinensis Root Extract, Lonicera Japonica (Honeysuckle) Flower Extract, Glycyrrhiza Glabra (Licorice) Root Extract, Zingiber Officinale (Ginger) Root Extract, Perilla Frutescens Leaf Extract, Pinus Palustris Leaf Extract, Methylchloroisothiazolinone.

PURPOSE

Purpose : Shampoo (cleaning hair and scalp)

WARNINGS

Warnings: 1. Discontinue to use this production if the below symptoms occure in use : Damage on the skin or scalp such as mucosa, scar or eczema. 2. In case of having following symptoms, consult the medical specialist before use. In case of having allergy(like red rash, swollenness, itching, dermatitis) caused by drug or cosmetics. 3. Immediately stop using and consult the medical specialist for below cases. (Consult with this affixation, if possible.) (a)In case of having problems such as red rash, swollenness, itching stimulation during usage (b) In case of having pruritis or pain. 4. Others caution in usage. (a)External use only.(Internal use forbidden.) (b)Be careful not to get it into your eyes and in case you have to wash it immediately and consult the medical specialist if the symptom gets worse. (c)Be careful of overuse so that the scalp could not lose its oil and it gets roughen. 5. Caution in storage (a)Protect from light and heat. Store in the shade. (b)Keep out of reach of children. (c)Causing accident or degradation from keeping in the different containers from the oriinal container, keep in the designated container with airtight lid.

KEEP OUT OF REACH OF CHILDREN

INDICATIONS & USAGE

Indications and usage: 1. Better to wash in the evening to get rid of foreign substances on the scalp accumulated during the day. 2. A through wash is required. 3. Dry in a mild-warm air 4. Wash face and/or shave with bubbles left on hair for 1 to 2 minutes before washing out. 5. Do not use rinse products while using O shampoo 6. Taking half-bath with bubbles on the hair makes you feel fresh.

DOSAGE & ADMINISTRATION

Dosage and administration: Use an adequate amount of this product Suggested use is once a day.